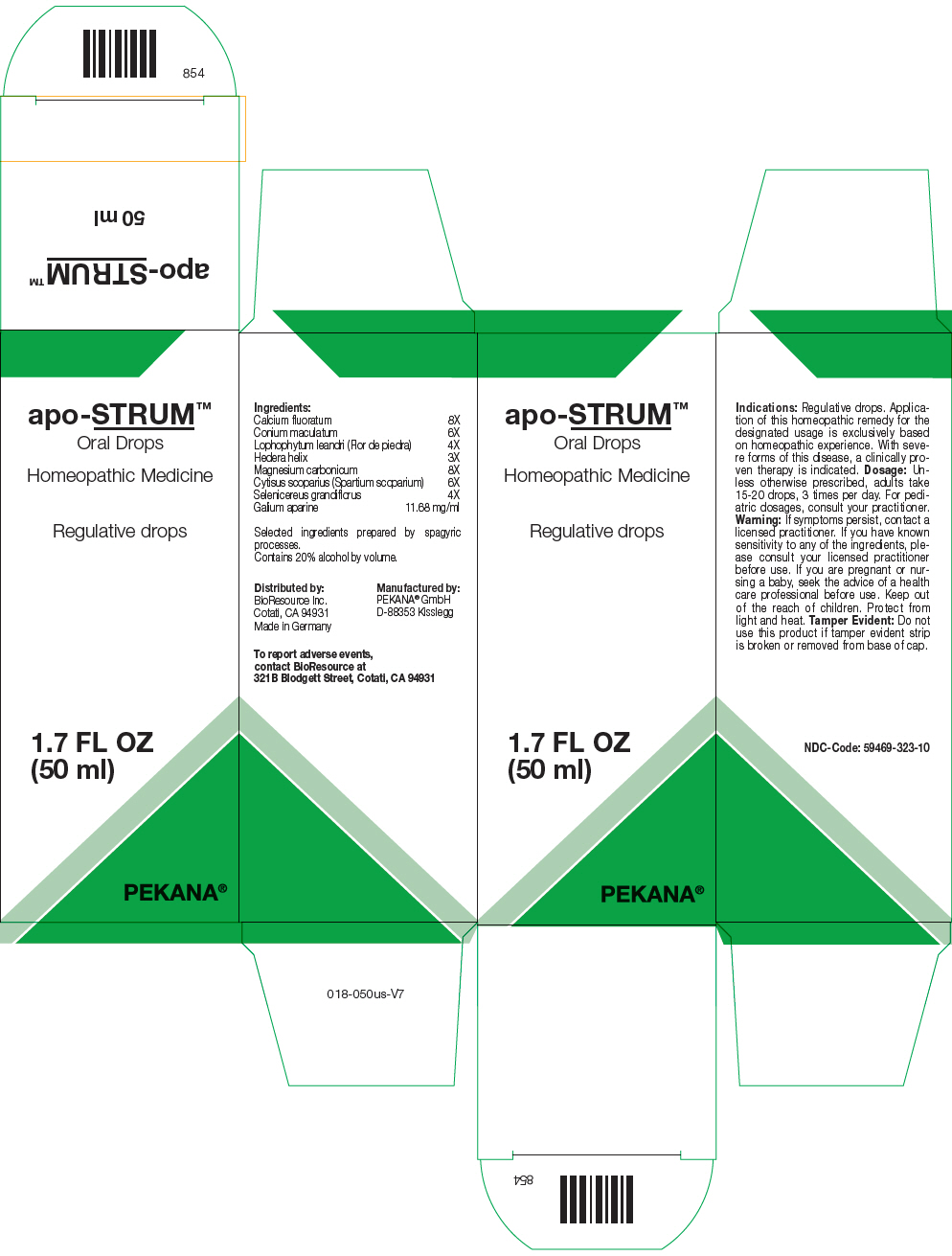 DRUG LABEL: apo-STRUM
NDC: 59469-323 | Form: SOLUTION/ DROPS
Manufacturer: PEKANA Naturheilmittel GmbH
Category: homeopathic | Type: HUMAN OTC DRUG LABEL
Date: 20230111

ACTIVE INGREDIENTS: CALCIUM FLUORIDE 8 [hp_X]/50 mL; CONIUM MACULATUM FLOWERING TOP 6 [hp_X]/50 mL; LOPHOPHYTUM LEANDRII 4 [hp_X]/50 mL; HEDERA HELIX FLOWERING TWIG 3 [hp_X]/50 mL; MAGNESIUM CARBONATE 8 [hp_X]/50 mL; CYTISUS SCOPARIUS FLOWERING TOP 6 [hp_X]/50 mL; SELENICEREUS GRANDIFLORUS WHOLE 4 [hp_X]/50 mL; GALIUM APARINE WHOLE 584 mg/50 mL
INACTIVE INGREDIENTS: WATER; ALCOHOL

apo-STRUM™

ACTIVE INGREDIENT

Ingredients:
Calcium fluoratum | 8X
Conium maculatum | 6X
Lophophytum leandri (Flor de piedra) | 4X
Hedera helix | 3X
Magnesium carbonicum | 8X
Cytisus scoparius (Spartium scoparium) | 6X
Selenicereus grandiflorus | 4X
Galium aparine | 11.68 mg/ml

Selected ingredients prepared by spagyric processes.

INACTIVE INGREDIENT

Contains 20% alcohol by volume.

Indications

PURPOSE

Regulative drops. Application of this homeopathic remedy for the designated usage is exclusively based on homeopathic experience. With severe forms of this disease, a clinically proven therapy is indicated.

Dosage

Unless otherwise prescribed, adults take 15-20 drops, 3 times per day. For pediatric dosages, consult your practitioner.

Warning

If symptoms persist, contact a licensed practitioner. If you have known sensitivity to any of the ingredients, please consult your licensed practitioner before use. If you are pregnant or nursing a baby, seek the advice of a health care professional before use.

Keep out of the reach of children.

STORAGE AND HANDLING

Protect from light and heat.

Tamper Evident

Do not use this product if tamper evident strip is broken or removed from base of cap.

QUESTIONS

To report adverse events, contact BioResource at 321B Blodgett Street, Cotati, CA 94931

Distributed by:
BioResource Inc.
Cotati, CA 94931

Manufactured by:
PEKANA® GmbH
D-88353 Kisslegg

PRINCIPAL DISPLAY PANEL - 50 ml Bottle Box

apo-STRUM™

Oral Drops

Homeopathic Medicine

Regulative drops

1.7 FL OZ
(50 ml)

PEKANA®